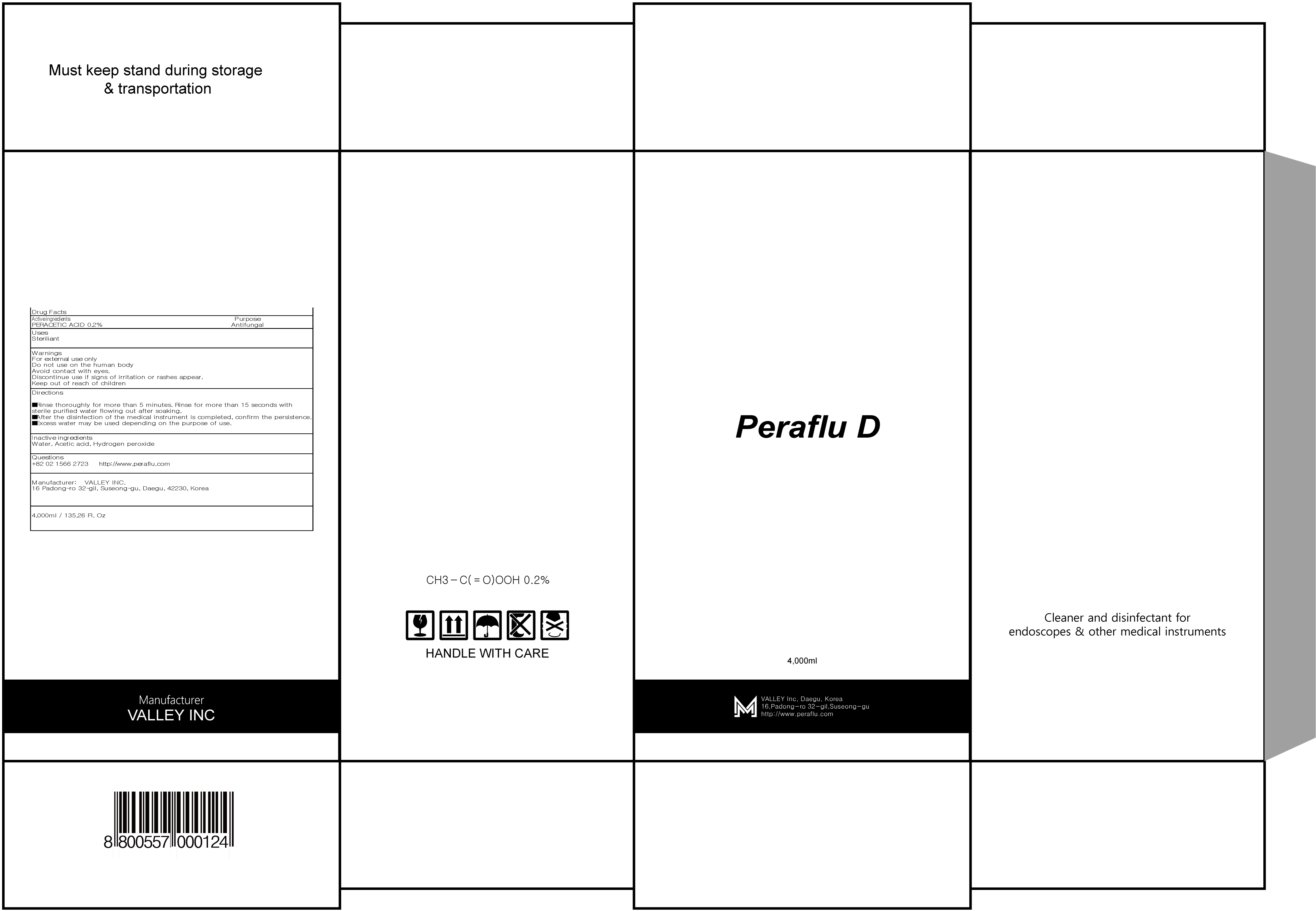 DRUG LABEL: Peraflu D
NDC: 81803-020 | Form: LIQUID
Manufacturer: Valley Inc.
Category: otc | Type: HUMAN OTC DRUG LABEL
Date: 20241209

ACTIVE INGREDIENTS: PERACETIC ACID 8 g/4000 mL
INACTIVE INGREDIENTS: WATER; ACETIC ACID

ACTIVE INGREDIENT

PERACETIC ACID 0.2%

INACTIVE INGREDIENTS

Water, Acetic acid, Hydrogen peroxide

PURPOSE

Antifungal

WARNINGS

For external use only

Do not use on the human body

Avoid contact with eyes.

Discontinue use if signs of irritation or rashes appear.

Keep out of reach of children

KEEP OUT OF REACH OF CHILDREN

Uses

Steriliant

Directions

- Rinse thoroughly for more than 5 minutes. Rinse for more than 15 seconds with sterile purified water flowing out after soaking.

- After the disinfection of the medical instrument is completed, confirm the persistence.

- Excess water may be used depending on the purpose of use.

QUESTIONS

+82 02 1566 2723

http://www.peraflu.com